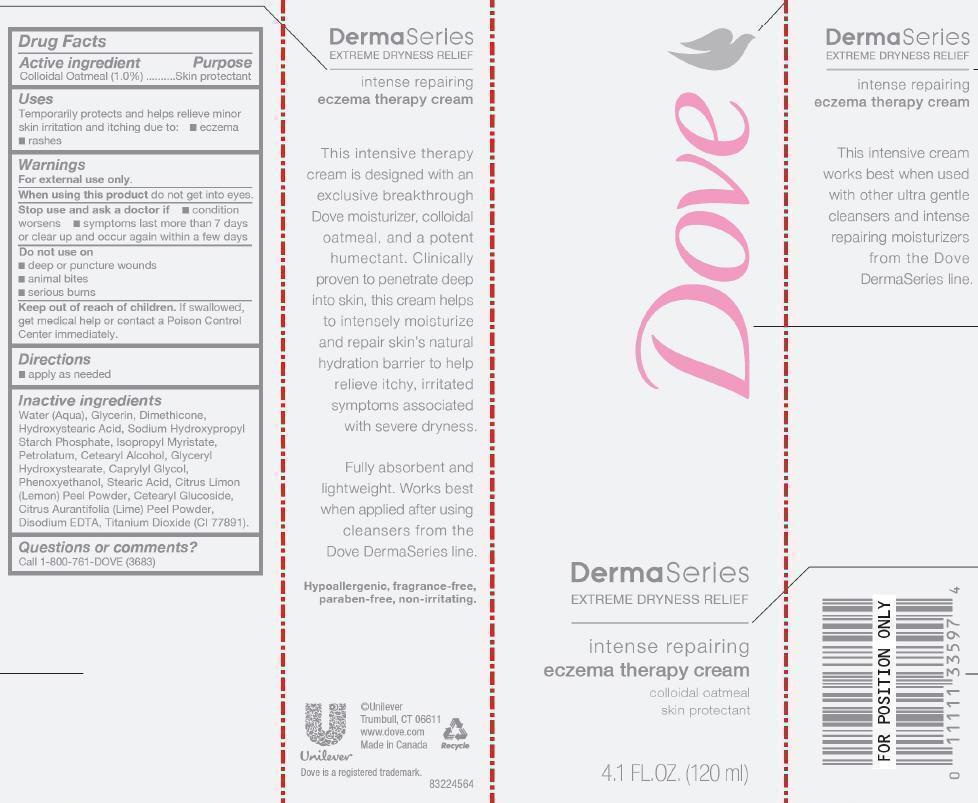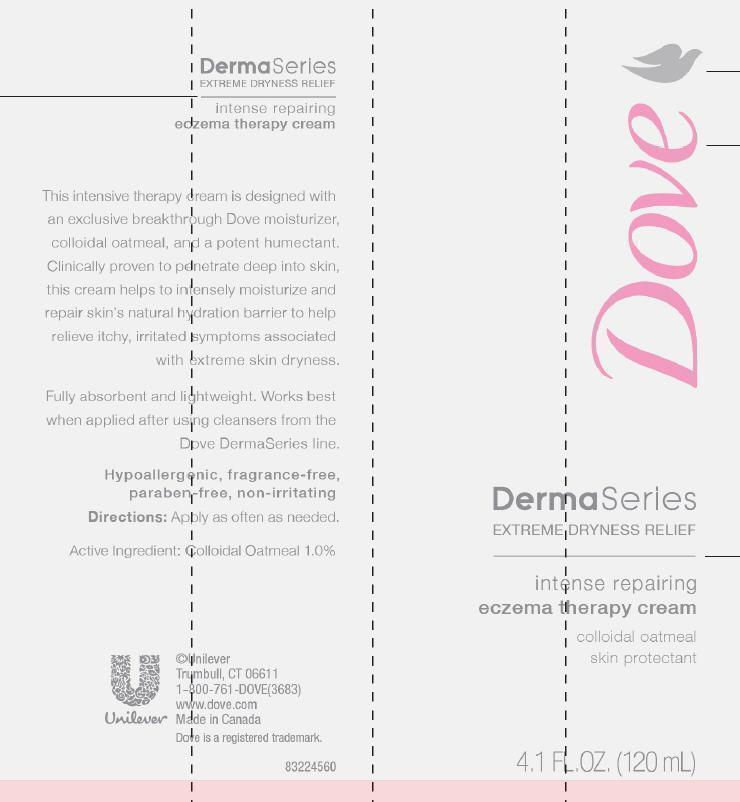 DRUG LABEL: Dove DermaSeries
NDC: 64942-1306 | Form: CREAM
Manufacturer: Conopco Inc. d/b/a Unilever
Category: otc | Type: HUMAN OTC DRUG LABEL
Date: 20221205

ACTIVE INGREDIENTS: OATMEAL 1 g/100 mL
INACTIVE INGREDIENTS: WATER; GLYCERIN; DIMETHICONE; 12-HYDROXYSTEARIC ACID; ISOPROPYL MYRISTATE; PETROLATUM; CETOSTEARYL ALCOHOL; CAPRYLYL GLYCOL; PHENOXYETHANOL; STEARIC ACID; LEMON PEEL; CETEARYL GLUCOSIDE; LIME PEEL; EDETATE DISODIUM; TITANIUM DIOXIDE

Dove DermaSeries Eczema Therapy Cream

Active ingredient

Colloidal Oatmeal (1.0%)

Purpose

Skin protectant

Uses

Temporarily protects and helps relieve minor skin irritation and itching due to: ● eczema rashes

WARNINGS
For External Use Only.

When using this product do not get into eyes.

Stop use and ask a doctor if ● condition worsens ● symptoms last more than 7 days or clear up and occur again within a few days

Do not use on

● deep or puncture wounds

● animal bites

● serious burns

Keep out of reach of children. If swallowed get medical help or contact a Poison Control Center immediately.

Directions

● apply as needed.

Inactive Ingredients

Water (Aqua), Glycerin, Dimethicone, Hydroxystearic Acid, Sodium Hydroxypropyl Starch Phosphate, Isopropyl Myristate, Petrolatum, Cetearyl Alcohol, Glyceryl Hydroxystearate, Caprylyl Glycol, Phenoxyethanol, Stearic Acid, Citrus Limon (Lemon) Peel Powder, Cetearyl Glucoside, Citrus Aurantifolia (Lime) Peel Powder, Disodium EDTA, Titanium Dioxide (CI 77891).

Questions or comments?

Call 1-800-761-DOVE (3683)